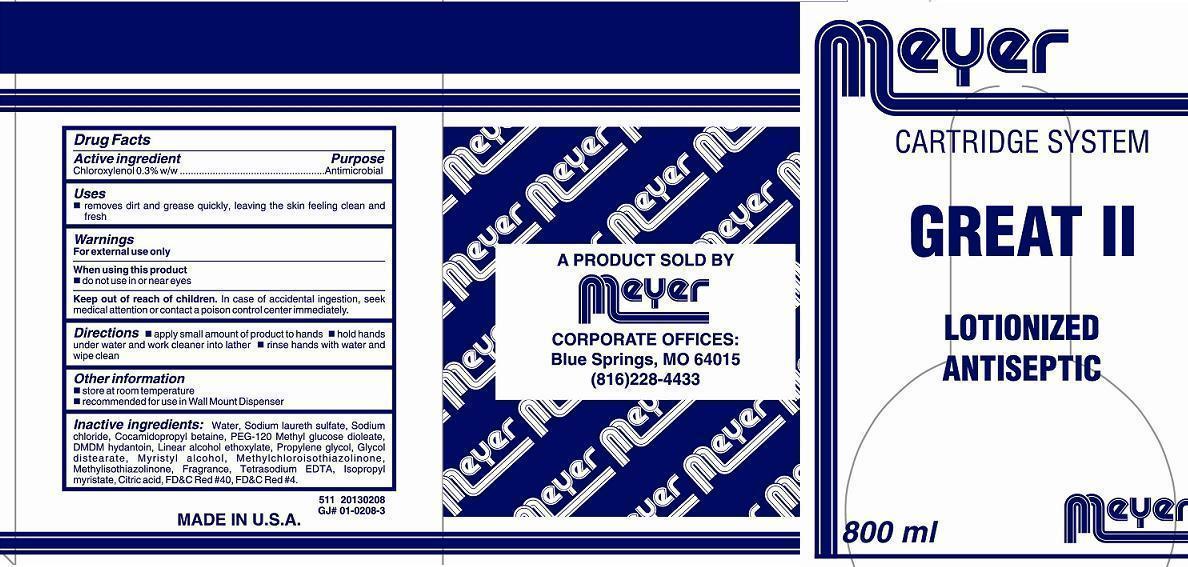 DRUG LABEL: GREAT II LOTIONIZED ANTISEPTIC
NDC: 59756-511 | Form: SOAP
Manufacturer: MEYER LABORATORY
Category: otc | Type: HUMAN OTC DRUG LABEL
Date: 20180207

ACTIVE INGREDIENTS: CHLOROXYLENOL 3 g/1000 mL
INACTIVE INGREDIENTS: WATER; GLYCOL DISTEARATE; MYRISTYL ALCOHOL; C9-11 PARETH-6; SODIUM LAURETH SULFATE; PROPYLENE GLYCOL; ISOPROPYL MYRISTATE; METHYLCHLOROISOTHIAZOLINONE; METHYLISOTHIAZOLINONE; COCAMIDOPROPYL BETAINE; DMDM HYDANTOIN; PEG-120 METHYL GLUCOSE DIOLEATE; EDETATE SODIUM; CITRIC ACID MONOHYDRATE; SODIUM CHLORIDE

Active ingredient

Chloroxylenol 0.3% w/w

Purpose

Antimicrobial

Keep out of reach of children

In case of accidental ingestion, seek medical attention or contact a poison control center immediately.

Uses

- removes dirt and grease quickly, leaving the skin feeling clean and fresh

Warnings

For external use only

When using this product

- do not use in or near eyes

Directions

 apply small amount of product to hands.  hold hands under water and work cleaner into lather.  rinse hands with water and wipe clean.

Other information

 store at room temperature

 recommended for use in Wall Mount Dispenser

Inactive ingredients:

Water, Sodium laureth sulfate, Sodium chloride, Cocamidopropyl betaine, PEG-120 Methyl glucose dioleate, DMDM hydantoin, Linear alcohol ethoxylate, Propylene glycol, Glycol distearate, Myristyl alcohol, Methylchloroisothiazolinone, Methylisothiazolinone, Fragrance, Tetrasodium EDTA, Isopropyl myristate, Citric acid, FD&C Red #40, FD&C Red #4.